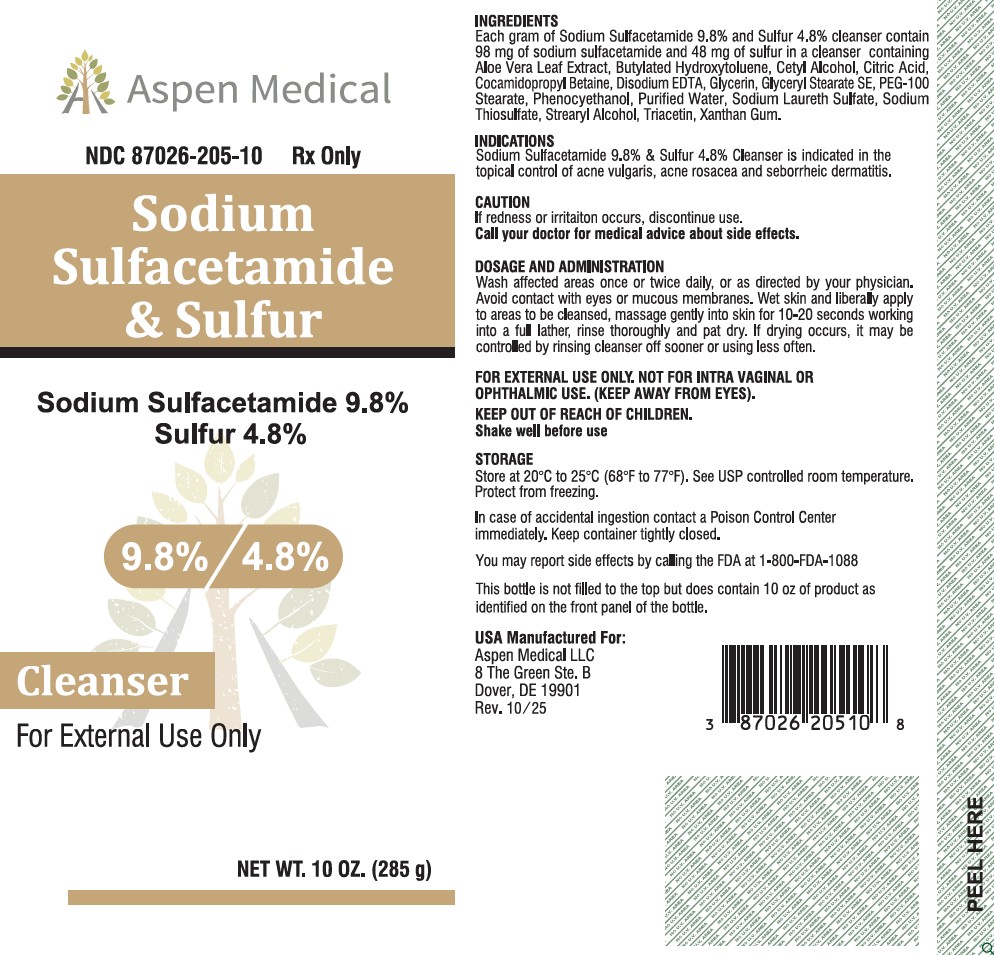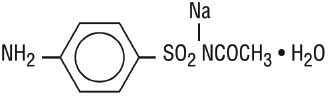 DRUG LABEL: SODIUM SULFACETAMIDE, SULFUR
NDC: 87026-205 | Form: LIQUID
Manufacturer: Aspen Medical LLC
Category: prescription | Type: HUMAN PRESCRIPTION DRUG LABEL
Date: 20260123

ACTIVE INGREDIENTS: SULFACETAMIDE SODIUM 98 mg/1 g; SULFUR 48 mg/1 g
INACTIVE INGREDIENTS: BUTYLATED HYDROXYTOLUENE; TRIACETIN; EDETATE DISODIUM; SODIUM THIOSULFATE; ALOE BARBADENSIS LEAF POWDER; GLYCERYL STEARATE SE; PHENOXYETHANOL; CETOSTEARYL ALCOHOL; COCAMIDOPROPYL BETAINE; WATER; CITRIC ACID; GLYCERIN; PEG-100 STEARATE; SODIUM LAURETH SULFATE; XANTHAN GUM

Sodium Sulfacetamide 9.8% Sulfur 4.8%

Rx Only

FOR EXTERNAL USE ONLY. NOT FOR INTRA VAGINAL OR OPHTHALMIC USE. (KEEP AWAY FROM EYES)

INACTIVE INGREDIENT

Aloe Vera Leaf Extract, Butylated Hydroxytoluene, Cetyl Alcohol, Citric Acid, Cocamidopropyl Betaine, Disodium EDTA, Glycerin, Glyceryl Stearate SE, PEG-100 Stearate, Phenocyethanol, Purified Water, Sodium Laureth Sulfate, Sodium Thiosulfate, Strearyl Alcohol, Triacetin, Xanthan Gum.

INDICATIONS AND USAGE

Sodium Sulfacetamide 9.8% & Sulfur 4.8% Cleanser is indicated in the topical control of acne vulgaris, acne rosacea and seborrheic dermatitis.

CAUTION

If redness or irritation occurs, discontinue use.

Call your doctor for medial advice about side effect.

DOSAGE AND ADMINISTRATION

Wash affected areas once or twice daily, or as directed by your physician. Avoid contact with eyes or mucous membranes. Wet skin and leberally apply to areas to be cleansed, massage gently into skin for 10-20 seconds working into a full leather, rinse thoroughly and pat dry. If drying occurs, it may be controlled by rinsing cleanser off sooner or using less often.

FOR EXTERNAL USE ONLY. NOT FOR INTRAVAGINAL OR OPTHALMIC USE. (KEEP AWAY FROM EYES).

KEEP OUT OF REACH OF CHILDREN

(Shake well before use)

STORAGE AND HANDLING

Store at 20°C to 25°C (68°F to 77°F). See USP controlled room temperature. Protect from freezing.

In case of accidental ingestion contact a Poison Control Center immediately. Keep container tightly closed.

You may report side effects by calling the FDA at 1-800-FDA-1088

DESCRIPTION

Sodium sulfacetamide is a sulfonamide with antibacterial activity while sulfur acts as a keratolytic agent. Chemically sodium sulfacetamide is N-[(4-aminophenyl)sulfonyl]-acetamide monosodium salt, monohydrate. The structural formula is:

CLINICAL PHARMACOLOGY

The most widely accepted mechanism of action of sulfonamides is the woods-fields theory which is based on the fact that sulfonamides act as competitive antagonists to para-aminobenzoic acid (PABA), an essential component for bacterial growth. While absorption through intact skin has not been determined, sodium sulfacetamide is readily absorbed from the gastrointestinal tract when taken orally and excreted in the urine, largely unchanged. The biological halflife has variously been reported as 7 to 12.8 hours. The exact mode of action of sulfur in the treatment of acne is unknown but it has been reported that it inhibits the growth of propionibacterium acnes and the formation of free fatty acids.

CONTRAINDICATIONS

Sodium Sulfacetamide 9.8% & Sulfur 4.8% Cleanser is contraindicated for use by patients having known hypersensitivity to sulfonamides, sulfur or any other component of this preparation. Sodium Sulfacetamide 9.8% & Sulfur 4.8% Cleanser is not to be used by patients with kidney disease.

WARNINGS

Although it is rare, sensitivity to sodium sulfacetamide may occur. Therefore, caution and careful supervision should be observed when prescribing this drug for patients who may be prone to hypersensitivity to topical sulfonamides. Systemic toxic reactions such as agranulocytosis, acute hemolytic anemia, purpura hemorrhagica, drug fever, jaundice, and contact dermatitis indicate hypersensitivity to sulfonamides. Particular caution should be employed if areas of denuded or abraded skin are involved.

GENERAL

If irritation develops, use of the product should be discontinued and appropriate therapy instituted. Patients should be carefully observed for possible local irritation or sensitization during long-term therapy. The object of this therapy is to achieve desquamation without irritation, but sodium sulfacetamide and sulfur can cause reddening and scaling of the epidermis. These side effects are not unusual in the treatment of acne vulgaris, but patients should be cautioned about the possibility.

INFORMATION FOR PATIENTS

Avoid contact with eyes, eyelids, lips and mucous membranes. If accidental contact occurs, rinse with water. If excessive irritation develops, discontinue use and consult your physician.

CARCINOGENESIS & MUTAGENESIS & IMPAIRMENT OF FERTILITY

Long-term studies in animals have not been performed to evaluate carcinogenic potential.

PREGNANCY Category C

Animal reproduction studies have not been conducted with Sodium Sulfacetamide 9.8% & Sulfur 4.8% Cleanser. It is also not known whether Sodium Sulfacetamide 9.8% & Sulfur 4.8% Cleanser can cause fetal harm when administered to a pregnant woman or can affect reproduction capacity. Sodium Sulfacetamide 9.8% & Sulfur 4.8% Cleanser should be given to a pregnant woman only if clearly needed.

PEDIATRIC USE

Safety and effectiveness in children under the age of 12 have not been established.

NURSING MOTHERS

It is not known whether sodium sulfacetamide is excreted in the human milk following topical use of Sodium Sulfacetamide 9.8% & Sulfur 4.8% Cleanser. However, small amounts of orally administered sulfonamides have milk. In view of this and because many drugs are excreted in human milk, caution should be exercised when Sodium Sulfacetamide 9.8% & Sulfur 4.8% Cleanser is administered to a nursing woman.

ADVERSE REACTIONS

Although rare, sodium sulfacetamide may cause local irritation.

HOW SUPPLIED

Sodium Sulfacetamide 9.8% & Sulfur 4.8 % Cleanser is available in

10 oz (285 g) bottle, NDC 87026-205-10.

This bottle is not filled to the top but does contain 10 oz of product as identified on the front panel of the bottle.

USA Manufactured For:

Aspen Medical LLC

8 The Green Ste. B

Dover, DE 19901

Rev. 10/25

PACKAGE LABEL

Aspen Medical

NDC 87026-205-10

Rx Only

Sodium

Sulfacetamide

& Sulfur

Sodium Sulfacetamide 9.8%

Sulfur 4.8%

9.8%/4.8%

Cleanser

For External Use only

NET WT. 10 OZ. (285 g)